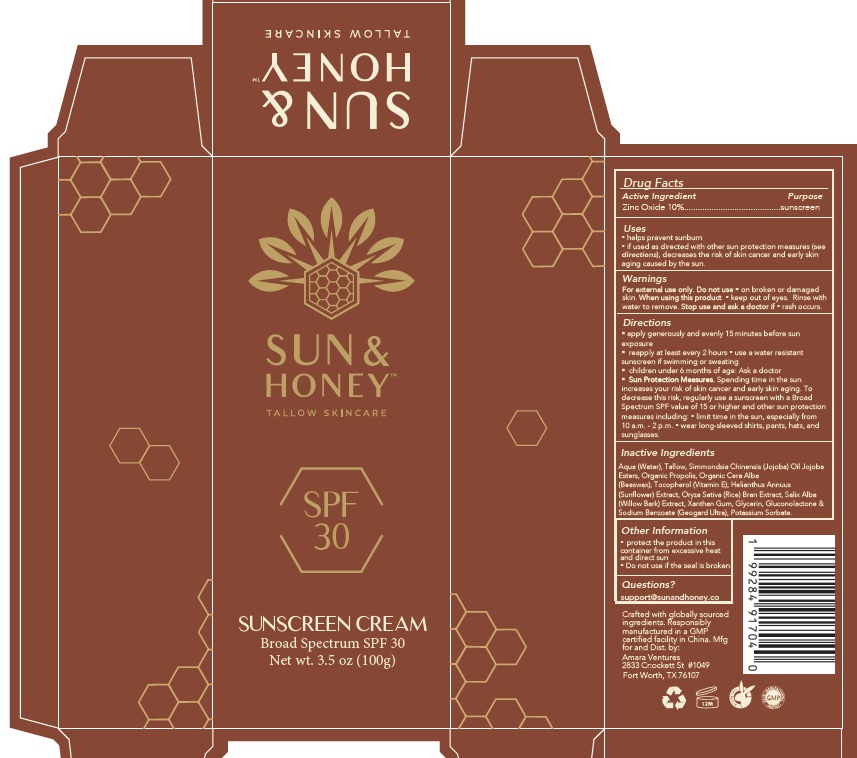 DRUG LABEL: Sun and Honey
NDC: 85432-001 | Form: CREAM
Manufacturer: Amara Ventures
Category: otc | Type: HUMAN OTC DRUG LABEL
Date: 20250408

ACTIVE INGREDIENTS: ZINC OXIDE 10 g/100 g
INACTIVE INGREDIENTS: WATER; TALLOW; SIMMONDSIA CHINENSIS (JOJOBA) SEED OIL; JOJOBA OIL, RANDOMIZED; PROPOLIS WAX; YELLOW WAX; TOCOPHEROL; SUNFLOWER SEED; RICE BRAN; SALIX ALBA BARK; XANTHAN GUM; GLYCERIN; GLUCONOLACTONE; SODIUM BENZOATE; POTASSIUM SORBATE

Active Ingredient Purpose

Zinc Oxide 10% sunscreen

Uses

- helps prevent sunburn
- if used as directed with other sun protection measures (see directions), decreases the risk of skin cancer and early skin aging caused by the sun.

Warnings

- For external use only.
- Do not useon broken or damaged skin.
- When using this product keep out of eyes. Rinse with water to remove.
- Stop use and ask a doctor ifrash occurs.

Directions

- apply generously and evenly 15 minutes before sun exposure
- reapply at least every 2 hours
- use a water resistant sunscreen if swimming or sweating
- children under 6 months of age: Ask a doctor
- Sun Protection Measures. Spending time in the sun increases your risk of skin cancer and early skin aging. To decrease this risk, regularly use a sunscreen with a Broad Spectrum SPF value of 15 or higher and other sun protection measures including:
- limit time in the sun, especially from 10 a.m. - 2 p.m.
- wear long-sleeved shirts, pants, hats, and sunglasses.

Inactive Ingredients

Aqua (Water), Tallow, Simmondsia Chinensis (Jojoba) Oil Jojoba Esters, Organic Propolis, Organic Cera Alba (Beeswax), Tocopherol (Vitamin E), Helianthus Annuus (Sunflower) Extract, Oryza Sativa (Rice) Bran Extract, Salix Alba (Willow Bark) Extract, Xanthan Gum, Glycerin, Gluconolactone & Sodium Benzoate (Geogard Ultra), Potassium Sorbate.

Other Information

- protect the product in this container from excessive heat and direct sun
- Do not use if the seal is broken